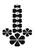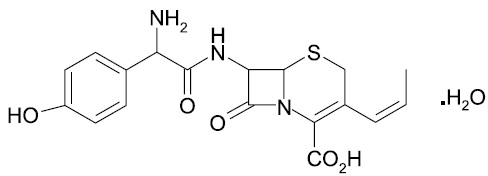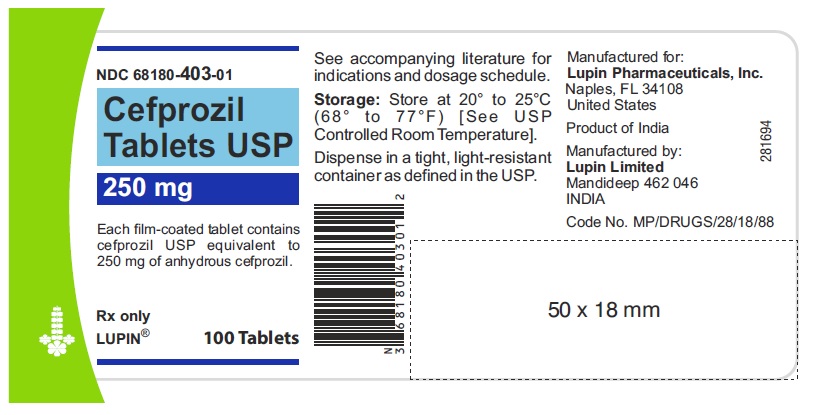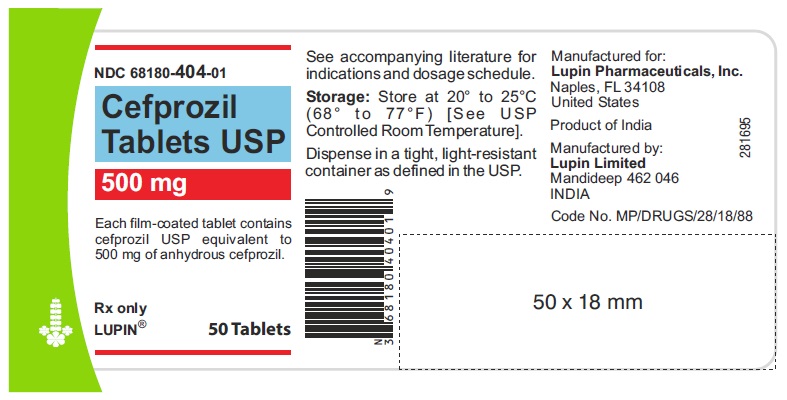 DRUG LABEL: CEFPROZIL
NDC: 68180-403 | Form: TABLET
Manufacturer: Lupin Pharmaceuticals, Inc.
Category: prescription | Type: HUMAN PRESCRIPTION DRUG LABEL
Date: 20251010

ACTIVE INGREDIENTS: CEFPROZIL 250 mg/1 1
INACTIVE INGREDIENTS: FD&C YELLOW NO. 6; SODIUM STARCH GLYCOLATE TYPE A POTATO; METHYLCELLULOSE (15 CPS); CELLULOSE, MICROCRYSTALLINE; MAGNESIUM STEARATE; TITANIUM DIOXIDE

CEFPROZIL TABLETS USP 250 mg and 500 mg
Rx Only

To reduce the development of drug-resistant bacteria and maintain the effectiveness of cefprozil tablets and other antibacterial drugs, cefprozil tablets should be used only to treat or prevent infections that are proven or strongly suspected to be caused by bacteria.

DESCRIPTION

Cefprozil is a semi-synthetic broad-spectrum cephalosporin antibiotic.

Cefprozil is a cis and trans isomeric mixture (≥90% cis). The chemical name for the monohydrate is (6R,7R)-7-[(R)-2-Amino-2-(p-hydroxyphenyl)acetamido]-8-oxo-3-propenyl-5-thia-1-azabicyclo[4.2.0]oct-2-ene-2- carboxylic acid monohydrate, and the structural formula is:

Cefprozil is a white to yellowish powder with a molecular formula for the monohydrate of C18H19N3O5S.H2O and a molecular weight of 407.45.

Cefprozil tablets are intended for oral administration.

Cefprozil tablets contain cefprozil equivalent to 250 mg or 500 mg of anhydrous cefprozil. In addition, each tablet contains the following inactive ingredients: magnesium stearate, methylcellulose, microcrystalline cellulose, sodium starch glycolate and titanium dioxide. The 250 mg tablet also contains FD & C Yellow No. 6 Aluminum Lake.

CLINICAL PHARMACOLOGY

The pharmacokinetic data were derived from the capsule formulation; however, bioequivalence has been demonstrated for the oral solution, capsule, tablet, and suspension formulations under fasting conditions.

Following oral administration of cefprozil to fasting subjects, approximately 95% of the dose was absorbed. The average plasma half-life in normal subjects was 1.3 hours, while the steady-state volume of distribution was estimated to be 0.23 L/kg. The total body clearance and renal clearance rates were approximately 3 mL/min/kg and 2.3 mL/min/kg, respectively.

Average peak plasma concentrations after administration of 250 mg, 500 mg, or 1 g doses of cefprozil to fasting subjects were approximately 6.1, 10.5, and 18.3 mcg/mL, respectively, and were obtained within 1.5 hours after dosing. Urinary recovery accounted for approximately 60% of the administered dose. (See Table.)

Dosage (mg) | Mean Plasma Cefprozil |  |  | 8 hour Urinary Excretion (%)
 | Concentrations (mcg/mL) [Data represent mean values of 12 healthy volunteers.]
 | Peak appx. 1.5 h | 4 h | 8 h
250 mg | 6.1 | 1.7 | 0.2 | 60%
500 mg | 10.5 | 3.2 | 0.4 | 62%
1000 mg | 18.3 | 8.4 | 1.0 | 54%

During the first 4 hour period after drug administration, the average urine concentrations following 250 mg, 500 mg, and 1 g doses were approximately 700 mcg/mL, 1000 mcg/mL, and 2900 mcg/mL, respectively.

Administration of cefprozil with food did not affect the extent of absorption (AUC) or the peak plasma concentration (Cmax) of cefprozil. However, there was an increase of 0.25 to 0.75 hours in the time to maximum plasma concentration of cefprozil (Tmax).

The bioavailability of the capsule formulation of cefprozil was not affected when administered 5 minutes following an antacid.

Plasma protein binding is approximately 36% and is independent of concentration in the range of 2 mcg/mL to 20 mcg/mL.

There was no evidence of accumulation of cefprozil in the plasma in individuals with normal renal function following multiple oral doses of up to 1000 mg every 8 hours for 10 days.

In patients with reduced renal function, the plasma half-life may be prolonged up to 5.2 hours depending on the degree of the renal dysfunction. In patients with complete absence of renal function, the plasma half-life of cefprozil has been shown to be as long as 5.9 hours. The half-life is shortened during hemodialysis. Excretion pathways in patients with markedly impaired renal function have not been determined. (See PRECAUTIONS and DOSAGE AND ADMINISTRATION.)

In patients with impaired hepatic function, the half-life increases to approximately 2 hours. The magnitude of the changes does not warrant a dosage adjustment for patients with impaired hepatic function.

Healthy geriatric volunteers (≥65 years old) who received a single 1 g dose of cefprozil had 35% to 60% higher AUC and 40% lower renal clearance values compared with healthy adult volunteers 20 to 40 years of age. The average AUC in young and elderly female subjects was approximately 15% to 20% higher than in young and elderly male subjects. The magnitude of these age- and gender-related changes in the pharmacokinetics of cefprozil is not sufficient to necessitate dosage adjustments.

Adequate data on CSF levels of cefprozil are not available.

Comparable pharmacokinetic parameters of cefprozil are observed between pediatric patients (6 months to 12 years) and adults following oral administration of selected matched doses. The maximum concentrations are achieved at 1 to 2 hours after dosing.

The plasma elimination half-life is approximately 1.5 hours. In general, the observed plasma concentrations of cefprozil in pediatric patients at the 7.5, 15, and 30 mg/kg doses are similar to those observed within the same time frame in normal adult subjects at the 250, 500, and 1000 mg doses, respectively. The comparative plasma concentrations of cefprozil in pediatric patients and adult subjects at the equivalent dose level are presented in the table below.

 |  | Mean (SD) Plasma Cefprozil
 |  | Concentrations (mcg/mL)
Population | Dose | 1 h | 2 h | 4 h | 6 h | T½ (h)
children | 7.5 mg/kg | 4.70 | 3.99 | 0.91 | 0.23 a | 0.94
(n=18) |  | (1.57) | (1.24) | (0.30) | (0.13) | (0.32)
adults | 250 mg | 4.82 | 4.92 | 1.70b | 0.53 | 1.28
(n=12) |  | (2.13) | (1.13) | (0.53) | (0.17) | (0.34)
children | 15 mg/kg | 10.86 | 8.47 | 2.75 | 0.61c | 1.24
(n=19) |  | (2.55) | (2.03) | (1.07) | (0.27) | (0.43)
adults | 500 mg | 8.39 | 9.42 | 3.18d | 1.00d | 1.29
(n=12) |  | (1.95) | (0.98) | (0.76) | (0.24) | (0.14)
children | 30 mg/kg | 16.69 | 17.61 | 8.66 | -- | 2.06
(n=10) |  | (4.26) | (6.39) | (2.70) |  | (0.21)
adults | 1000 mg | 11.99 | 16.95 | 8.36 | 2.79 | 1.27
(n=12) |  | (4.67) | (4.07) | (4.13) | (1.77) | (0.12)
an=11 bn=5 cn=9 dn=11

Microbiology:

Cefprozil has in vitro activity against a broad range of gram-positive and gram-negative bacteria. The bactericidal action of cefprozil results from inhibition of cell-wall synthesis. Cefprozil has been shown to be active against most strains of the following microorganisms both in vitro and in clinical infections as described in the INDICATIONS AND USAGEsection.

Aerobic Gram-Positive Microorganisms:

Staphylococcus aureus

(including ß-lactamase-producing strains)

NOTE: Cefprozil is inactive against methicillin-resistant staphylococci.

Streptococcus pneumoniae

Streptococcus pyogenes

Aerobic Gram-Negative Microorganisms:

Haemophilus influenzae

(including ß-lactamase-producing strains)

Moraxella (Branhamella) catarrhalis

(including ß-lactamase-producing strains)

The following in vitro data are available; however, their clinical significance is unknown. Cefprozil exhibits in vitro minimum inhibitory concentrations (MICs) of 8 mcg/mL or less against most (≥90%) strains of the following microorganisms; however, the safety and effectiveness of cefprozil in treating clinical infections due to these microorganisms have not been established in adequate and well-controlled clinical trials.

Aerobic Gram-Positive Microorganisms:

Enterococcus durans

Enterococcus faecalis

Listeria monocytogenes

Staphylococcus epidermidis

Staphylococcus saprophyticus

Staphylococcus warneri

Streptococcus agalactiae

Streptococci (Groups C, D, F, and G)

viridans group Streptococci

NOTE: Cefprozil is inactive against Enterococcus faecium .

Aerobic Gram-Negative Microorganisms:

Citrobacter diversus

Escherichia coli

Klebsiella pneumoniae

Neisseria gonorrhoeae

(including ß-lactamase-producing strains)

Proteus mirabilis

Salmonella spp.

Shigella spp .

Vibrio spp.

NOTE: Cefprozil is inactive against most strains of Acinetobacter, Enterobacter, Morganella morganii, Proteus vulgaris, Providencia, Pseudomonas, and Serratia.

Anaerobic Microorganisms:

Prevotella (Bacteroides) melaninogenicus

Clostridium difficile

Clostridium perfringens

Fusobacterium spp.

Peptostreptococcus spp.

Propionibacterium acnes

NOTE: Most strains of the Bacteroides fragilis group are resistant to cefprozil.

Susceptibility Tests:

Dilution Techniques: Quantitative methods are used to determine antimicrobial minimal inhibitory concentrations (MICs). These MICs provide estimates of the susceptibility of bacteria to antimicrobial compounds. The MICs should be determined using a standardized procedure. Standardized procedures are based on a dilution method^1,2 (broth or agar) or equivalent with standardized inoculum concentrations and standardized concentrations of cefprozil powder. The MIC values should be interpreted according to the following criteria:

MIC (mcg/mL) | Interpretation
≤8 | Susceptible (S)
16 | Intermediate (I)
≥32 | Resistant (R)

A report of "Susceptible" indicates that the pathogen is likely to be inhibited if the antimicrobial compound in the blood reaches the concentrations usually achievable. A report of "Intermediate" indicates that the result should be considered equivocal, and, if the microorganism is not fully susceptible to alternative, clinically feasible drugs, the test should be repeated. This category implies possible clinical applicability in body sites where the drug is physiologically concentrated or in situations where high dosage of drug can be used. This category also provides a buffer zone which prevents small uncontrolled technical factors from causing major discrepancies in interpretation. A report of "Resistant" indicates that the pathogen is not likely to be inhibited if the antimicrobial compound in the blood reaches the concentrations usually achievable; other therapy should be selected.

Standardized susceptibility test procedures require the use of laboratory control microorganisms to control the technical aspects of the laboratory procedures. Standard cefprozil powder should provide the following MIC values:

Microorganism | MIC (mcg/mL)
Enterococcus faecalis ATCC 29212 | 4 to 16
Escherichia coli ATCC 25922 | 1 to 4
Haemophilus influenzae ATCC 49766 | 1 to 4
Staphylococcus aureus ATCC 29213 | 0.25 to 1
Streptococcus pneumoniae ATCC 49619 | 0.25 to 1

Diffusion Techniques: Quantitative methods that require measurement of zone diameters also provide reproducible estimates of the susceptibility of bacteria to antimicrobial compounds. One such standardized procedure^3 requires the use of standardized inoculum concentrations. This procedure uses paper disks impregnated with 30 mcg cefprozil to test the susceptibility of microorganisms to cefprozil.

Reports from the laboratory providing results of the standard single-disk susceptibility test with a 30-mcg cefprozil disk should be interpreted according to the following criteria:

Zone diameter (mm) | Interpretation
≥18 | Susceptible (S)
15 to 17 | Intermediate (I)
≤14 | Resistant (R)

Interpretation should be as stated above for results using dilution techniques. Interpretation involves correlation of the diameter obtained in the disk test with the MIC for cefprozil.

As with standardized dilution techniques, diffusion methods require the use of laboratory control microorganisms that are used to control the technical aspects of the laboratory procedures. For the diffusion technique, the 30-mcg cefprozil disk should provide the following zone diameters in these laboratory test quality control strains.

Microorganism | Zone diameter (mm)
Escherichia coli ATCC 25922 | 21 to 27
Haemophilus influenzae ATCC 49766 | 20 to 27
Staphylococcus aureus ATCC 25923 | 27 to 33
Streptococcus pneumoniae ATCC 49619 | 25 to 32

INDICATIONS AND USAGE

Cefprozil tablets are indicated for the treatment of patients with mild to moderate infections caused by susceptible strains of the designated microorganisms in the conditions listed below:

Upper Respiratory Tract:

Pharyngitis/Tonsillitis:

Caused by Streptococcus pyogenes.

NOTE: The usual drug of choice in the treatment and prevention of streptococcal infections, including the prophylaxis of rheumatic fever, is penicillin given by the intramuscular route. Cefprozil is generally effective in the eradication of Streptococcus pyogenes from the nasopharynx; however, substantial data establishing the efficacy of cefprozil in the subsequent prevention of rheumatic fever are not available at present.

Otitis Media:

Caused by Streptococcus pneumoniae, Haemophilus influenzae (including ß-lactamase-producing strains), and Moraxella (Branhamella) catarrhalis (including ß-lactamase-producing strains). (See CLINICAL STUDIES.)

NOTE: In the treatment of otitis media due to ß-lactamase producing organisms, cefprozil had bacteriologic eradication rates somewhat lower than those observed with a product containing a specific ß-lactamase inhibitor. In considering the use of cefprozil, lower overall eradication rates should be balanced against the susceptibility patterns of the common microbes in a given geographic area and the increased potential for toxicity with products containing ß-lactamase inhibitors.

Acute Sinusitis:

Caused by Streptococcus pneumoniae, Haemophilus influenzae (including ß-lactamase producing strains), and Moraxella (Branhamella) catarrhalis (including ß-lactamase-producing strains).

Lower Respiratory Tract:

Acute Bacterial Exacerbation of Chronic Bronchitis:

Caused by Streptococcus pneumoniae, Haemophilus influenzae (including ß-lactamase-producing strains), and Moraxella (Branhamella) catarrhalis (including ß-lactamase-producing strains).

Skin and Skin Structure:

Uncomplicated Skin and Skin-Structure Infections:

Caused by Staphylococcus aureus (including penicillinase-producing strains) and Streptococcus pyogenes. Abscesses usually require surgical drainage.

To reduce the development of drug-resistant bacteria and maintain the effectiveness of cefprozil tablets and other antibacterial drugs, cefprozil tablets should be used only to treat or prevent infections that are proven or strongly suspected to be caused by susceptible bacteria. When culture and susceptibility information are available, they should be considered in selecting or modifying antibacterial therapy. In the absence of such data, local epidemiology and susceptibility patterns may contribute to the empiric selection of therapy.

CONTRAINDICATIONS

Cefprozil is contraindicated in patients with known allergy to the cephalosporin class of antibiotics.

WARNINGS

BEFORE THERAPY WITH CEFPROZIL IS INSTITUTED, CAREFUL INQUIRY SHOULD BE MADE TO DETERMINE WHETHER THE PATIENT HAS HAD PREVIOUS HYPERSENSITIVITY REACTIONS TO CEFPROZIL, CEPHALOSPORINS, PENICILLINS, OR OTHER DRUGS. IF THIS PRODUCT IS TO BE GIVEN TO PENICILLIN-SENSITIVE PATIENTS, CAUTION SHOULD BE EXERCISED BECAUSE CROSS-SENSITIVITY AMONG ß-LACTAM ANTIBIOTICS HAS BEEN CLEARLY DOCUMENTED AND MAY OCCUR IN UP TO 10% OF PATIENTS WITH A HISTORY OF PENICILLIN ALLERGY. IF AN ALLERGIC REACTION TO CEFPROZIL OCCURS, DISCONTINUE THE DRUG. SERIOUS ACUTE HYPERSENSITIVITY REACTIONS MAY REQUIRE TREATMENT WITH EPINEPHRINE AND OTHER EMERGENCY MEASURES, INCLUDING OXYGEN, INTRAVENOUS FLUIDS, INTRAVENOUS ANTIHISTAMINES, CORTICOSTEROIDS, PRESSOR AMINES, AND AIRWAY MANAGEMENT, AS CLINICALLY INDICATED.

Clostridium difficile associated diarrhea (CDAD) has been reported with use of nearly all antibacterial agents, including Cefprozil, and may range in severity from mild diarrhea to fatal colitis. Treatment with antibacterial agents alters the normal flora of the colon leading to overgrowth of C. difficile.

C. difficile produces toxins A and B which contribute to the development of CDAD. Hypertoxin-producing strains of C. difficile cause increased morbidity and mortality, as these infections can be refractory to antimicrobial therapy and may require colectomy. CDAD must be considered in all patients who present with diarrhea following antibiotic use. Careful medical history is necessary since CDAD has been reported to occur over two months after the administration of antibacterial agents.

If CDAD is suspected or confirmed, ongoing antibiotic use not directed against C. difficile may need to be discontinued. Appropriate fluid and electrolyte management, protein supplementation, antibiotic treatment of C. difficile, and surgical evaluation should be instituted as clinically indicated.

PRECAUTIONS

General:

Prescribing cefprozil in the absence of proven or strongly suspected bacterial infection or a prophylactic indication is unlikely to provide benefit to the patient and increases the risk of the development of drug-resistant bacteria.

In patients with known or suspected renal impairment (see DOSAGE AND ADMINISTRATION),careful clinical observation and appropriate laboratory studies should be done prior to and during therapy. The total daily dose of cefprozil should be reduced in these patients because high and/or prolonged plasma antibiotic concentrations can occur in such individuals from usual doses. Cephalosporins, including cefprozil, should be given with caution to patients receiving concurrent treatment with potent diuretics since these agents are suspected of adversely affecting renal function.

Prolonged use of cefprozil may result in the overgrowth of nonsusceptible organisms. Careful observation of the patient is essential. If superinfection occurs during therapy, appropriate measures should be taken.

Cefprozil should be prescribed with caution in individuals with a history of gastrointestinal disease particularly colitis.

Positive direct Coombs' tests have been reported during treatment with cephalosporin antibiotics.

Information for Patients:

Patients should be counseled that antibacterial drugs including cefprozil should only be used to treat bacterial infections. They do not treat viral infections (e.g., the common cold). When cefprozil are prescribed to treat a bacterial infection, patients should be told that although it is common to feel better early in the course of therapy, the medication should be taken exactly as directed. Skipping doses or not completing the full course of therapy may (1) decrease the effectiveness of the immediate treatment and (2) increase the likelihood that bacteria will develop resistance and will not be treatable by cefprozil or other antibacterial drugs in the future.

Diarrhea is a common problem caused by antibiotics which usually ends when the antibiotic is discontinued. Sometimes after starting treatment with antibiotics, patients can develop watery and bloody stools (with or without stomach cramps and fever) even as late as two or more months after having taken the last dose of the antibiotic. If this occurs, patients should contact their physician as soon as possible.

Drug Interactions:

Nephrotoxicity has been reported following concomitant administration of aminoglycoside antibiotics and cephalosporin antibiotics. Concomitant administration of probenecid doubled the AUC for cefprozil.

The bioavailability of the capsule formulation of cefprozil was not affected when administered 5 minutes following an antacid.

Drug/Laboratory Test Interactions:

Cephalosporin antibiotics may produce a false positive reaction for glucose in the urine with copper reduction tests (Benedict’s or Fehling’s solution or with Clinitest® tablets), but not with enzyme-based tests for glycosuria (e.g., Clinistix®). A false negative reaction may occur in the ferricyanide test for blood glucose. The presence of cefprozil in the blood does not interfere with the assay of plasma or urine creatinine by the alkaline picrate method.

Carcinogenesis, Mutagenesis, Impairment of Fertility:

Long term in vivo studies have not been performed to evaluate the carcinogenic potential of cefprozil.

Cefprozil was not found to be mutagenic in either the Ames Salmonella or E. coli WP2 urvA reversion assays or the Chinese hamster ovary cell HGPRT forward gene mutation assay and it did not induce chromosomal abnormalities in Chinese hamster ovary cells or unscheduled DNA synthesis in rat hepatocytes in vitro. Chromosomal aberrations were not observed in bone marrow cells from rats dosed orally with over 30 times the highest recommended human dose based upon mg/m^2.

Impairment of fertility was not observed in male or female rats given oral doses of cefprozil up to 18.5 times the highest recommended human dose based upon mg/m^2.

Pregnancy:

Teratogenic Effects- Pregnancy Category B:

Reproduction studies have been performed in rabbits, mice, and rats using oral doses of cefprozil of 0.8, 8.5, and 18.5 times the maximum daily human dose (1000 mg) based upon mg/m^2, and have revealed no harm to the fetus. There are, however, no adequate and well-controlled studies in pregnant women. Because animal reproduction studies are not always predictive of human response, this drug should be used during pregnancy only if clearly needed.

Labor and Delivery:

Cefprozil has not been studied for use during labor and delivery. Treatment should only be given if clearly needed.

Nursing Mothers:

Small amounts of cefprozil (<0.3% of dose) have been detected in human milk following administration of a single 1 gram dose to lactating women. The average levels over 24 hours ranged from 0.25 to 3.3 mcg/mL. Caution should be exercised when cefprozil tablets are administered to a nursing woman, since the effect of cefprozil on nursing infants is unknown.

Pediatric Use:

(See INDICATIONS AND USAGEand DOSAGE AND ADMINISTRATION.)

The safety and effectiveness of cefprozil in the treatment of otitis media have been established in the age groups 6 months to 12 years. Use of cefprozil for the treatment of otitis media is supported by evidence from adequate and well-controlled studies of cefprozil in pediatric patients. (See CLINICAL STUDIES)

The safety and effectiveness of cefprozil in the treatment of pharyngitis/tonsillitis or uncomplicated skin and skin-structure infections have been established in the age groups 2 to 12 years. Use of cefprozil for the treatment of these infections is supported by evidence from adequate and well-controlled studies of cefprozil in pediatric patients.

The safety and effectiveness of cefprozil in the treatment of acute sinusitis have been established in the age groups 6 months to 12 years. Use of cefprozil in these age groups is supported by evidence from adequate and well-controlled studies of cefprozil in adults.

Safety and effectiveness in pediatric patients below the age of 6 months have not been established for the treatment of otitis media or acute sinusitis, or below the age of 2 years for the treatment of pharyngitis/tonsillitis or uncomplicated skin and skin-structure infections. However, accumulation of other cephalosporin antibiotics in newborn infants (resulting from prolonged drug half-life in this age group) has been reported.

Geriatric Use:

Of the more than 4500 adults treated with cefprozil in clinical studies, 14% were 65 years and older, while 5% were 75 years and older. When geriatric patients received the usual recommended adult doses, their clinical efficacy and safety were comparable to clinical efficacy and safety in nongeriatric adult patients. Other reported clinical experience has not identified differences in responses between elderly and younger patients, but greater sensitivity of some older individuals to the effects of cefprozil cannot be excluded (see CLINICAL PHARMACOLOGY).

Cefprozil is known to be substantially excreted by the kidney, and the risk of toxic reactions to this drug may be greater in patients with impaired renal function. Because elderly patients are more likely to have decreased renal function, care should be taken in dose selection and it may be useful to monitor renal function. See DOSAGE AND ADMINISTRATION for dosing recommendations for patients with impaired renal function.

ADVERSE REACTIONS

The adverse reactions to cefprozil are similar to those observed with other orally administered cephalosporins. Cefprozil was usually well tolerated in controlled clinical trials. Approximately 2% of patients discontinued cefprozil therapy due to adverse events.

The most common adverse effects observed in patients treated with cefprozil are:

Gastrointestinal:

Diarrhea (2.9%), nausea (3.5%), vomiting (1%), and abdominal pain (1%).

Hepatobiliary:

Elevations of AST (SGOT) (2%), ALT (SGPT) (2%), alkaline phosphatase (0.2%), and bilirubin values (<0.1%). As with some penicillins and some other cephalosporin antibiotics, cholestatic jaundice has been reported rarely.

Hypersensitivity:

Rash (0.9%), urticaria (0.1%). Such reactions have been reported more frequently in children than in adults. Signs and symptoms usually occur a few days after initiation of therapy and subside within a few days after cessation of therapy.

CNS:

Dizziness (1%), hyperactivity, headache, nervousness, insomnia, confusion, and somnolence have been reported rarely (<1%). All were reversible.

Hematopoietic:

Decreased leukocyte count (0.2%), eosinophilia (2.3%).

Renal:

Elevated BUN (0.1%), serum creatinine (0.1%).

Other:

Diaper rash and superinfection (1.5%), genital pruritus and vaginitis (1.6%).

The following adverse events, regardless of established causal relationship to cefprozil tablets, have been rarely reported during postmarketing surveillance: anaphylaxis, angioedema, colitis (including pseudomembranous colitis), erythema multiforme, fever, serumsickness like reactions, Stevens-Johnson syndrome, and thrombocytopenia.

Cephalosporin Class Paragraph:

In addition to the adverse reactions listed above which have been observed in patients treated with cefprozil, the following adverse reactions and altered laboratory tests have been reported for cephalosporin-class antibiotics:

Aplastic anemia, hemolytic anemia, hemorrhage, renal dysfunction, toxic epidermal necrolysis, toxic nephropathy, prolonged prothrombin time, positive Coombs’ test, elevated LDH, pancytopenia, neutropenia, agranulocytosis.

Several cephalosporins have been implicated in triggering seizures, particularly in patients with renal impairment, when the dosage was not reduced. (See DOSAGE AND ADMINISTRATION and OVERDOSAGE.)If seizures associated with drug therapy occur, the drug should be discontinued. Anticonvulsant therapy can be given if clinically indicated.

OVERDOSAGE

Single 5000 mg/kg oral doses of cefprozil caused no mortality or signs of toxicity in adult, weanling, or neonatal rats, or adult mice. A single oral dose of 3000 mg/kg caused diarrhea and loss of appetite in cynomolgus monkeys, but no mortality.

Cefprozil is eliminated primarily by the kidneys. In case of severe overdosage, especially in patients with compromised renal function, hemodialysis will aid in the removal of cefprozil from the body.

DOSAGE AND ADMINISTRATION

Cefprozil tablets are administered orally.

Population/Infection | Dosage (mg) | Duration (days)
ADULTS (13 years and older)
UPPER RESPIRATORY TRACT
Pharyngitis/Tonsillitis | 500 q24h | 10 a
Acute Sinusitis | 250 q12h or | 10
(For moderate to severe infections, the higher dose should be used) | 500 q12h
LOWER RESPIRATORY TRACT
Acute Bacterial Exacerbation of Chronic Bronchitis | 500 q12h | 10
SKIN AND SKIN STRUCTURE
Uncomplicated Skin and Skin Structure Infections | 250 q12h or | 10
 | 500 q24h or
 | 500 q12h
CHILDREN (2 years to 12 years)
UPPER RESPIRATORY TRACT b
Pharyngitis/Tonsillitis | 7.5 mg/kg q12h | 10 a
SKIN AND SKIN STRUCTURE
Uncomplicated Skin and Skin Structure Infections | 20 mg/kg q24h | 10
INFANTS & CHILDREN (6 months to 12 years)
UPPER RESPIRATORY TRACTb
Otitis Media | 15 mg/kg q12h | 10
(See INDICATIONS AND USAGE and CLINICAL STUDIES)
Acute Sinusitis | 7.5 mg/kg q12h or | 10
(For moderate to severe infections, the higher dose should be used) | 15 mg/kg q12h
a In the treatment of infections due to Streptococcus pyogenes, cefprozil tablets should be administered for at least 10 days.
b Not to exceed recommended adult doses.

Renal Impairment:

Cefprozil may be administered to patients with impaired renal function. The following dosage schedule should be used.

Creatinine Clearance (mL/min) | Dosage (mg) | Dosing Interval
30 to 120 | standard | standard
0 to 29 [Cefprozil is in part removed by hemodialysis; therefore, cefprozil should be administered after the completion of hemodialysis.] | 50% of standard | standard

Hepatic Impairment:

No dosage adjustment is necessary for patients with impaired hepatic function.

HOW SUPPLIED

Cefprozil tablets USP, 250 mg and 500 mg are available as follows:

Each light orange, film-coated, oval tablet debossed with 'LUPIN' on one side and '250' on the other side, contains the equivalent of 250 mg anhydrous cefprozil.

Bottles of 100 Tablets NDC 68180-403-01

Each white, film-coated, oval tablet debossed with 'LUPIN' on one side and '500' on the other side, contains the equivalent of 500 mg anhydrous cefprozil.

Bottles of 50 Tablets NDC 68180-404-01

Store at 20° to 25°C (68° to 77°F) [See USP Controlled Room Temperature].

CLINICAL STUDIES

Study One:

In a controlled clinical study of acute otitis media performed in the United States where significant rates of ß-lactamase- producing organisms were found, cefprozil was compared to an oral antimicrobial agent that contained a specific ß-lactamase inhibitor. In this study, using very strict evaluability criteria and microbiologic and clinical response criteria at the 10 to 16 days post-therapy follow-up, the following presumptive bacterial eradication/clinical cure outcomes (i.e., clinical success) and safety results were obtained:

U.S. Acute Otitis Media Study

Cefprozil vs β-lactamase inhibitor-containing control drug

EFFICACY:

Pathogen | % of Cases with Pathogen (n=155) | Outcome
S. pneumoniae | 48.4% | cefprozil success rate 5% better than control
H. influenzae | 35.5% | cefprozil success rate 17% less than control
M. catarrhalis | 13.5% | cefprozil success rate 12% less than control
S. pyogenes | 2.6% | cefprozil equivalent to control
Overall | 100.0% | cefprozil success rate 5% less than control

SAFETY:

The incidences of adverse events, primarily diarrhea and rash*, were clinically and statistically significantly higher in the control arm versus the cefprozil arm.

Age Group | Cefprozil | Control
6 months to 2 years | 21% | 41%
3 to 12 years | 10% | 19%
*The majority of these involved the diaper area in young children.

Study Two:

In a controlled clinical study of acute otitis media performed in Europe, cefprozil was compared to an oral antimicrobial agent that contained a specific ß-lactamase inhibitor. As expected in a European population, this study population had a lower incidence of ß-lactamase-producing organisms than usually seen in U.S. trials. In this study, using very strict evaluability criteria and microbiologic and clinical response criteria at the 10 to 16 days post-therapy follow-up, the following presumptive bacterial eradication/clinical cure outcomes (i.e., clinical success) were obtained:

European Acute Otitis Media Study

Cefprozil vs β-lactamase inhibitor-containing control drug

EFFICACY:

Pathogen | % of Cases with Pathogen (n=47) | Outcome
S. pneumoniae | 51.0% | cefprozil equivalent to control
H. influenzae | 29.8% | cefprozil equivalent to control
M. catarrhalis | 6.4% | cefprozil equivalent to control
S. pyogenes | 12.8% | cefprozil equivalent to control
Overall | 100.0% | cefprozil equivalent to control

SAFETY:

The incidence of adverse events in the cefprozil arm was comparable to the incidence of adverse events in the control arm (agent that contained a specific ß-lactamase inhibitor).

REFERENCES

1. National Committee for Clinical Laboratory Standards. Methods for Dilution Antimicrobial Susceptibility Tests for Bacteria that Grow Aerobically-Third Edition. Approved Standard NCCLS Document M7-A3, Vol.13, No. 25, NCCLS, Villanova, PA, December 1993.
2. National Committee for Clinical Laboratory Standards. Methods for Antimicrobial Susceptibility Testing of Anaerobic Bacteria-Third Edition. Approved Standard NCCLS Document M11-A3, Vol. 13, No. 26, NCCLS, Villanova, PA, December 1993.
3. National Committee for Clinical Laboratory Standards. Performance Standards for Antimicrobial Disk Susceptibility Tests -Fifth Edition. Approved Standard NCCLS Document M2-A5, Vol. 13, No. 24, NCCLS, Villanova, PA, December 1993.

Clintest® and Clinistix® are registered trademarks of Bayer HealthCare LLC.

LUPIN and the are registered trademarks of Lupin Pharmaceuticals, Inc.

Manufactured for:

Lupin Pharmaceuticals, Inc.

Naples, FL 34108

United States

Manufactured by:

Lupin Limited

Mandideep 462046

INDIA

Revised: August 2024 ID#: 275964

PACKAGE LABEL

CEFPROZIL TABLETS USP

Rx Only

250 mg

NDC 68180-403-01

100 Tablets

CEFPROZIL TABLETS USP

Rx Only

500 mg

NDC 68180-404-01

50 Tablets